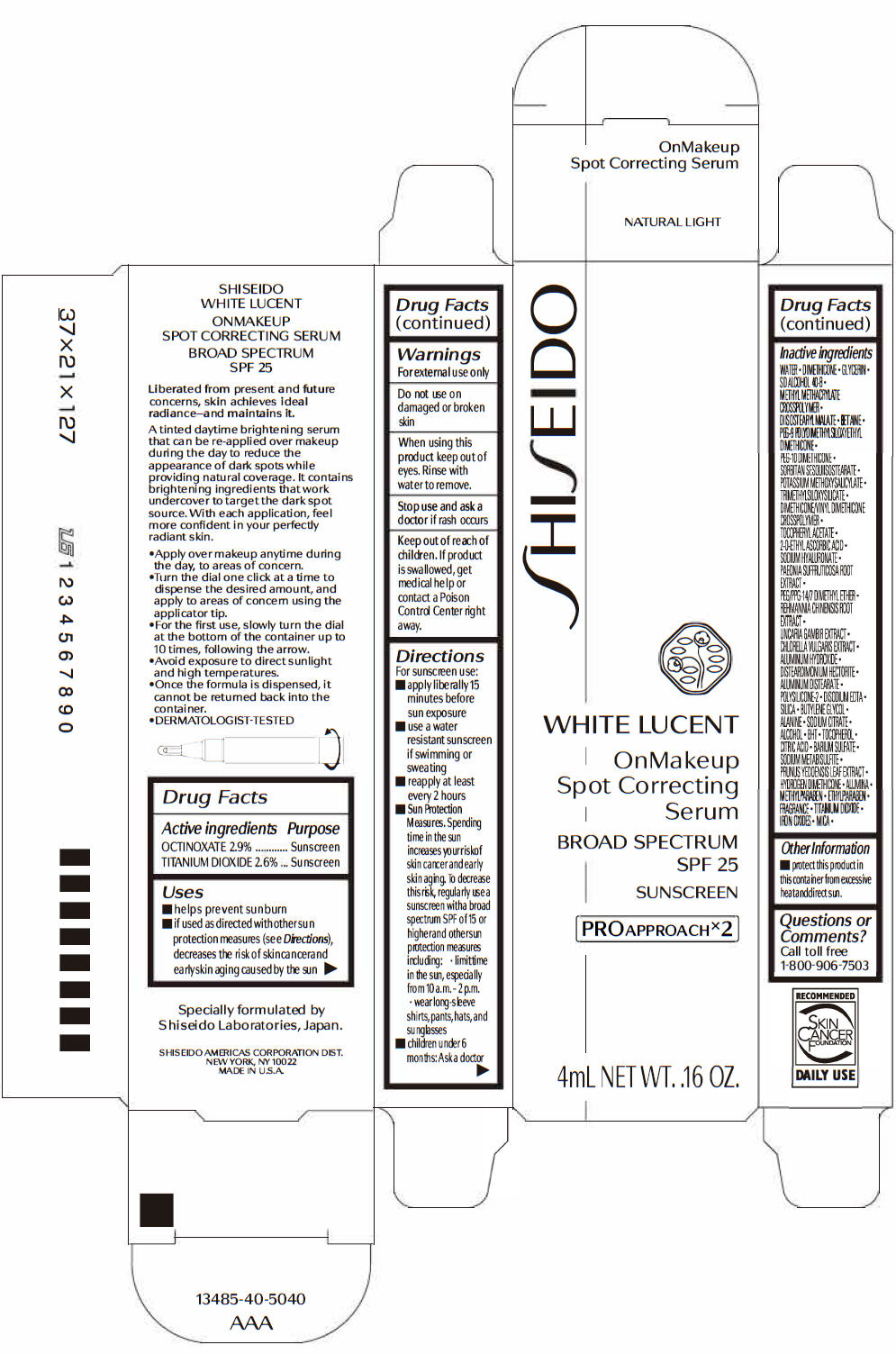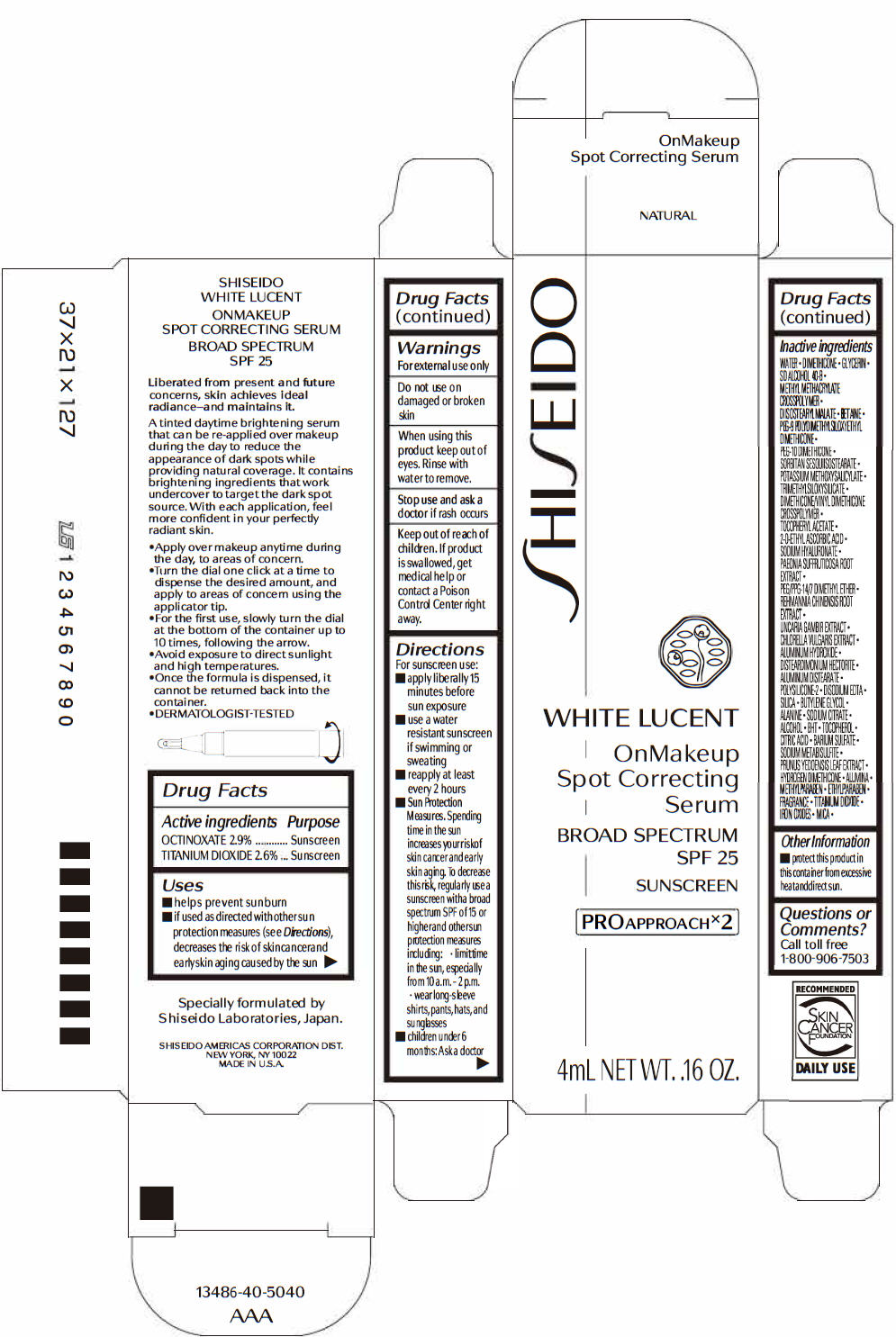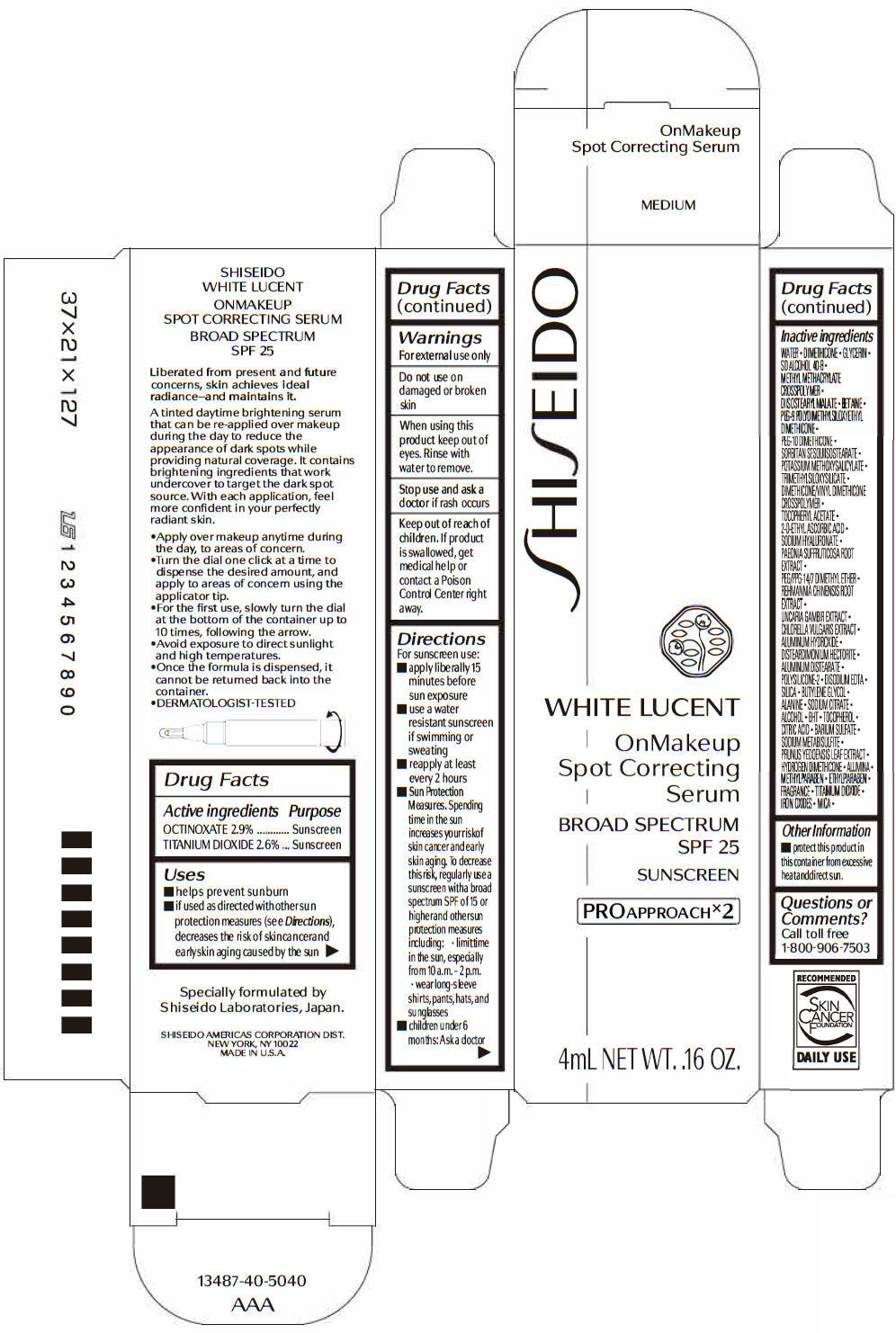 DRUG LABEL: SHISEIDO WHITE LUCENT ONMAKEUP SPOT CORRECTING SERUM
NDC: 58411-296 | Form: CREAM
Manufacturer: SHISEIDO AMERICAS CORPORATION
Category: otc | Type: HUMAN OTC DRUG LABEL
Date: 20260105

ACTIVE INGREDIENTS: OCTINOXATE 138 mg/4 mL; TITANIUM DIOXIDE 123 mg/4 mL
INACTIVE INGREDIENTS: WATER; DIMETHICONE; GLYCERIN; DIISOSTEARYL MALATE; BETAINE; PEG-9 POLYDIMETHYLSILOXYETHYL DIMETHICONE; PEG-10 DIMETHICONE (600 CST); POTASSIUM METHOXYSALICYLATE; TRIMETHYLSILOXYSILICATE (M/Q 0.6-0.8); DIMETHICONE/VINYL DIMETHICONE CROSSPOLYMER (SOFT PARTICLE); .ALPHA.-TOCOPHEROL ACETATE, DL-; 2-O-ETHYL ASCORBIC ACID; HYALURONATE SODIUM; PAEONIA X SUFFRUTICOSA ROOT; PEG/PPG-14/7 DIMETHYL ETHER; REHMANNIA GLUTINOSA ROOT; CHLORELLA VULGARIS; ALUMINUM HYDROXIDE; DISTEARDIMONIUM HECTORITE; ALUMINUM DISTEARATE; EDETATE DISODIUM; SILICON DIOXIDE; BUTYLENE GLYCOL; ALANINE; SODIUM CITRATE, UNSPECIFIED FORM; ALCOHOL; BUTYLATED HYDROXYTOLUENE; .ALPHA.-TOCOPHEROL; CITRIC ACID MONOHYDRATE; BARIUM SULFATE; SODIUM METABISULFITE; PRUNUS X YEDOENSIS LEAF; HYDROGEN DIMETHICONE (13 CST); ALUMINUM OXIDE; METHYLPARABEN; ETHYLPARABEN; FERRIC OXIDE RED; FERRIC OXIDE YELLOW; FERROSOFERRIC OXIDE; MICA

SHISEIDO WHITE LUCENT ONMAKEUP SPOT CORRECTING SERUM

Drug Facts

ACTIVE INGREDIENT

Active ingredients | Purpose
OCTINOXATE 2.9% | Sunscreen
TITANIUM DIOXIDE 2.6% | Sunscreen

Uses

- helps prevent sunburn
- if used as directed with other sun protection measures (see Directions), decreases the risk of skin cancer and early skin aging caused by the sun

Warnings

For external use only

Do not useon damaged or broken skin

WHEN USING

When using this productkeep out of eyes. Rinse with water to remove.

Stop use and ask a doctorif rash occurs

Keep out of reach of children.If product is swallowed, get medical help or contact a Poison Control Center right away.

Directions

- apply liberally 15 minutes before sun exposure
- use a water resistant sunscreen if swimming or sweating
- reapply at least every 2 hours
- Sun Protection Measures. Spending time in the sun increases your risk of skin cancer and early skin aging. To decrease this risk, regularly use a sunscreen with a broad spectrum SPF of 15 or higher and other sun protection measures including:
  - limit time in the sun, especially from 10 a.m. – 2 p.m.
  - wear long-sleeve shirts, pants, hats, and sunglasses
- children under 6 months: Ask a doctor

Inactive Ingredients

WATER•DIMETHICONE•GLYCERIN•SD ALCOHOL 40-B•METHYL METHACRYLATE CROSSPOLYMER•DIISOSTEARYL MALATE•BETAINE•PEG-9 POLYDIMETHYLSILOXYETHYL DIMETHICONE•PEG-10 DIMETHICONE•SORBITAN SESQUIISOSTEARATE•POTASSIUM METHOXYSALICYLATE•TRIMETHYLSILOXYSILICATE•DIMETHICONE/VINYL DIMETHICONE CROSSPOLYMER•TOCOPHERYL ACETATE•2-O-ETHYL ASCORBIC ACID•SODIUM HYALURONATE•PAEONIA SUFFRUTICOSA ROOT EXTRACT•PEG/PPG-14/7 DIMETHYL ETHER•REHMANNIA CHINENSIS ROOT EXTRACT•UNCARIA GAMBIR EXTRACT•CHLORELLA VULGARIS EXTRACT•ALUMINUM HYDROXIDE•DISTEARDIMONIUM HECTORITE•ALUMINUM DISTEARATE•POLYSILICONE-2•DISODIUM EDTA•SILICA•BUTYLENE GLYCOL•ALANINE•SODIUM CITRATE•ALCOHOL•BHT･TOCOPHEROL•CITRIC ACID•BARIUM SULFATE•SODIUM METABISULFITE•PRUNUS YEDOENSIS LEAF EXTRACT•HYDROGEN DIMETHICONE•ALUMINA•METHYLPARABEN•ETHYLPARABEN･FRAGRANCE•TITANIUM DIOXIDE•IRON OXIDES•MICA•

Other information

- protect this product in this container from excessive heat and direct sun.

Questions or comments?

Call toll free 1-800-906-7503

PRINCIPAL DISPLAY PANEL - 4 mL Bottle Carton - Natural Light

SHI SEIDO

WHITE LUCENT

OnMakeup
Spot Correcting
Serum

BROAD SPECTRUM
SPF 25

SUNSCREEN

PROAPPROACH× 2

4mL NET WT. .16 OZ.

PRINCIPAL DISPLAY PANEL - 4 mL Bottle Carton - Natural

SHI SEIDO

WHITE LUCENT

OnMakeup
Spot Correcting
Serum

BROAD SPECTRUM
SPF 25

SUNSCREEN

PROAPPROACH× 2

4mL NET WT. .16 OZ.

PRINCIPAL DISPLAY PANEL - 4 mL Bottle Carton - Medium

SHI SEIDO

WHITE LUCENT

OnMakeup
Spot Correcting
Serum

BROAD SPECTRUM
SPF 25

SUNSCREEN

PROAPPROACH× 2

4mL NET WT. .16 OZ.